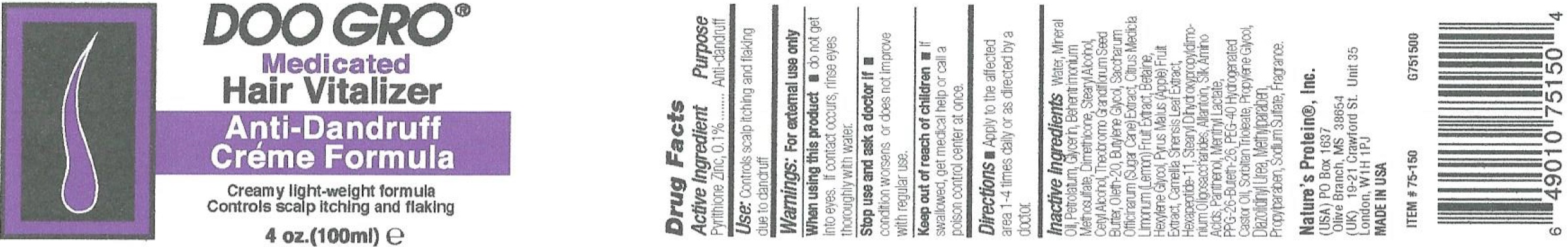 DRUG LABEL: Doo Gro Anti-Dandruff  Vitalizer
NDC: 12022-005 | Form: CREAM
Manufacturer: J. Strickland & Co. DBA Nature's Protein, Inc.
Category: otc | Type: HUMAN OTC DRUG LABEL
Date: 20231031

ACTIVE INGREDIENTS: PYRITHIONE ZINC 1 mg/1 mL
INACTIVE INGREDIENTS: WATER; MINERAL OIL; PETROLATUM; GLYCERIN; BEHENTRIMONIUM METHOSULFATE; DIMETHICONE; STEARYL ALCOHOL; CETYL ALCOHOL; THEOBROMA GRANDIFLORUM SEED BUTTER; OLETH-20; BUTYLENE GLYCOL; SUGARCANE; LEMON; BETAINE; HEXYLENE GLYCOL; APPLE; GREEN TEA LEAF; HEXAPEPTIDE-11; ALLANTOIN; AMINO ACIDS, SILK; PANTHENOL; MENTHYL LACTATE, (-)-; PPG-26-BUTETH-26; POLYOXYL 40 HYDROGENATED CASTOR OIL; SORBITAN TRIOLEATE; PROPYLENE GLYCOL; DIAZOLIDINYL UREA; METHYLPARABEN; PROPYLPARABEN; SODIUM SULFATE

Doo Gro Anti-Dandruff Cream Vitalizer

Active Ingredient

Pyrithione Zinc, 0.1%

Purpose

Anti-dandruff

Use:

Controls Scalp itching and flaking due to dandruff

Warnings:

For external use only

When using this product

- do not get into eyes. If contact occurs, rinse eyes thoroughly with water.

Stop use and ask a doctor if

- condition worsens or does not improve with regular use

Keep out of reach of children

- if swallowed, get medical help or call a poison control center at once.

Directions

- Apply to the affected area 1-4 times daily or as directed by a doctor.

Inactive Ingredients

Water, Mineral Oil, Petrolatum, Glycerin, Behentrimonium Methosulfate, Dimethicone, Stearyl Alcohol, Cetyl alcohol, Theobroma Grandiflorum Seed Butter, Oleth-20, Butylene Glycol, Saccharum Officinarum (Sugar Cane) Extract, Citrus Medica Limonum (Lemon) Fruit Extract, Betaine, Hexylene Glycol, Pyrus Malus (Apple) Fruit Extract, Camellia Sinensis Leaf Extract, Hexapeptide-11, Stearyl Dhydroxypropyldimonium Oligosaccharides, Allantoin, Silk Amino Acids, Panthenol, Menthyl Lactate, PPG-26-Buteth-26, PEG-40 Hydrogenated Castor Oil, Sorbitan Trioleate, Propylene Glycol, Diazolidinyl Urea, Methylparaben, Propylparaben, Sodium Sulfate, Fragrance.